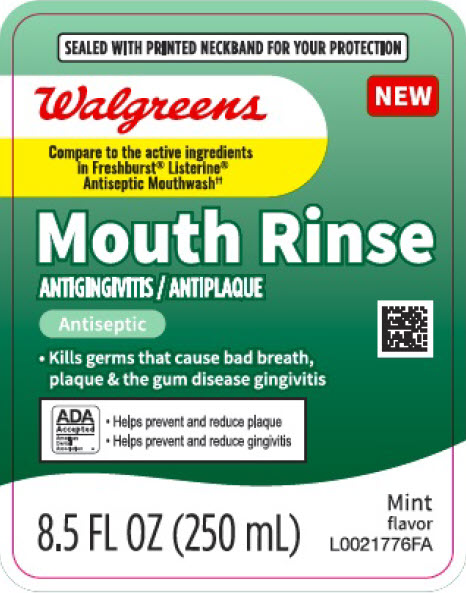 DRUG LABEL: Antiseptic Mouth Rinse
NDC: 0363-0072 | Form: MOUTHWASH
Manufacturer: Walgreen Co.
Category: otc | Type: HUMAN OTC DRUG LABEL
Date: 20260212

ACTIVE INGREDIENTS: EUCALYPTOL 0.92 mg/1 mL; MENTHOL 0.42 mg/1 mL; METHYL SALICYLATE 0.6 mg/1 mL; THYMOL 0.64 mg/1 mL
INACTIVE INGREDIENTS: WATER; ALCOHOL; SORBITOL SOLUTION; POLOXAMER 407; BENZOIC ACID; SACCHARIN SODIUM; SODIUM CITRATE; D&C YELLOW NO. 10; FD&C GREEN NO. 3

Walgreens 072.003/072AL rev 2-072AN
Spring Mint Antiseptic Mouthrinse

Active ingredients

Eucalyptol 0.092%

Menthol 0.042%

Methyl salicylate 0.060%

Thymol 0.064%

Purpose

Antigingivitis, Antiplaque

Use

helps control plaque that leads to gingivitis

Warnings

for this product

Do not use

If you have painful or swollen gums, pus from the gum line, loose teeth or increased spacing between the teeth. See your dentist immediately. These may be signs of periodontitis, a serious form of gum disease.

Stop use and ask a dentist if

Gingivitis, bleeding or redness persists for more than 2 weeks

Keep out of reach of children.

If more than used for rinsing is accidentally swallowed, get medical help or contact a Poison Control Center right away.

Directions

- do not swallow
- not intended to replace brushing or flossing

Adults and children 12 years of age and older - Vigorously swish 20 ml (2/3 FL OZ or 4 teaspoonfuls) between teeth twice a day for 30 seconds then spit out
Children under 12 years of age - Consult a dentist or doctor

Other information

Store at room temperature (59⁰ - 77⁰F)

Inactive ingredients

water, alcohol 21.6%, sorbitol, poloxamer 407, benzoic acid, sodium saccharin, flavor, sodium citrate, yellow 10, green 3

ADVERSE REACTIONS

‡This product is not manufactured or distributed by Kenvue, Inc., distributor of Freshburst® Listerine® Antiseptic Mouthwash.

DISTRIBUTED BY: WALGREEN CO.

200 WILMOT RD., DEERFIELD, IL 60015

walgreens.com 1-800-925-4733

W3ORG0924-F

DSP-TN-21081 DSP-MO-80087

ITEM 771870 W10100-1024-F

principal display panel

SEALED WITH PRINTED NECKBAND FOR YOUR PROTECTION

Walgreens

NEW

Compare to the active ingredients in Freshburst® Listerine® Antiseptic Mouthwash‡

Mouth Rinse

ANTIGINGIVITIS/ANTIPLAQUE

Antiseptic

- Kills germs that cause bad breath, plaque & the gum disease gingivitis

ADA Accepted

American Dental Association

- Helps prevent and reduce plaque
- Helps prevent and reduce gingivitis

8.5 FL OZ (250 mL)

Mint flavor